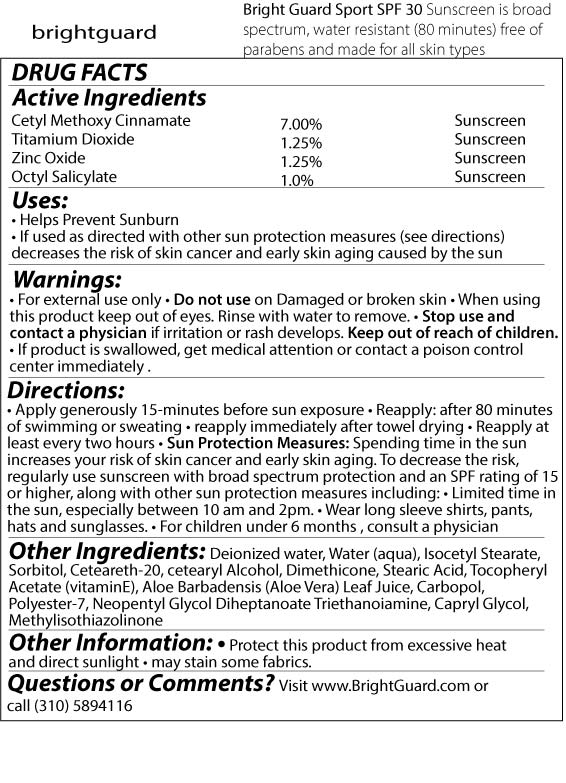 DRUG LABEL: Bright Guard Sport SPF
NDC: 76348-675 | Form: LOTION
Manufacturer: RENU LABORATORIES, LLC
Category: otc | Type: HUMAN OTC DRUG LABEL
Date: 20250512

ACTIVE INGREDIENTS: ZINC OXIDE 17.5 g/1000 g; OCTINOXATE 70 g/1000 g; OCTISALATE 10 g/1000 g; TITANIUM DIOXIDE 12.5 g/1000 g
INACTIVE INGREDIENTS: SORBITOL; POLYOXYL 20 CETOSTEARYL ETHER; CETOSTEARYL ALCOHOL; DIMETHICONE 350; CETYL ALCOHOL; STEARIC ACID; CARBOMER 934; WATER; ISOCETYL STEARATE; ALPHA-TOCOPHEROL ACETATE; TROLAMINE; ALOE VERA LEAF; POLYESTER-7; NEOPENTYL GLYCOL DIHEPTANOATE; CAPRYLYL GLYCOL; PHENOXYETHANOL; HEXYLENE GLYCOL

Bright Guard Sport SPF 30

STATEMENT OF IDENTITY

Bright Guard Sport SPF 30

sunscreen is broad spectrum, water

resistant (80 minutes), free of parabens

and made for all skin types

Active Ingredients

Octyl Methoxy Cinnamate 7.00% Sunscreen

Titanium Dioxide 1.25% Sunscreen

Zinc Oxide 1.25% Sunscreen

Octyl Salicylate 1.00% Sunscreen

Purpose

Octyl Methoxy Cinnamate 7.00% Sunscreen

Titanium Dioxide 1.25% Sunscreen

Zinc Oxide 1.25% Sunscreen

Octyl Salicylate 1.00% Sunscreen

USES

*Helps prevent sunburn.

*If used as directed with other sun protection measures (see directions), decreases the risk of skin cancer and early skin aging caused by the sun.

WARNINGS

- For external use only.
- Do not use on damaged or broken skin.
- When using this product keep out of eyes. Rinse with water to remove.
- Stop use and consult physician if irritation or rash develops.
- If product is swallowed, get medical attention or contact poison control center immediately.

Keep out of reach of children

DIRECTIONS

- Apply generously 15 minutes before sun exposure
- Reapply after 80 minutes of swimming or sweating.
- reapply immediately after towel drying.
- Reapply at least every 2 hours.
- Sun Protection Measures - Spending time in the sun increases your risk of skin cancer and early skin aging. To decrease this risk, regularly use sunscreen with broad spectrum protection and an SPF rating of 15 or higher, along with other sun protection measures including
- Limited time in the sun, especially between 10am and 2pm.
- Wear long sleeve shirts, pants, hats and sunglasses.
- For children under 6 months, consult a physician.

OTHER INGREDIENTS

Aloe Barbadensis (Aloe Vera) Leaf Juice, Caprylyl Glycol, Carbopol, Deionized Water, Ceteareth-20, Cetearyl Alcohol, Dimethicone, Isocetyl Stearate, Polyester-7, Neopentyl Glycol, Diheptanoate, Sorbitol, Stearic Acid, Tocopheryl Acetate (Vitamin E), Triethanolamine.

Other information

- Protect this product from excessive heat and direct sunlight.
- May stain some fabrics.

Questions or Comments?

Visit www.BrightGuard.com or call (310) 589-4116

KEEP OUT OF REACH OF CHILDREN

Pouch Label

BRIGHT GUARD SPORT SPF 30 POUCH LABEL